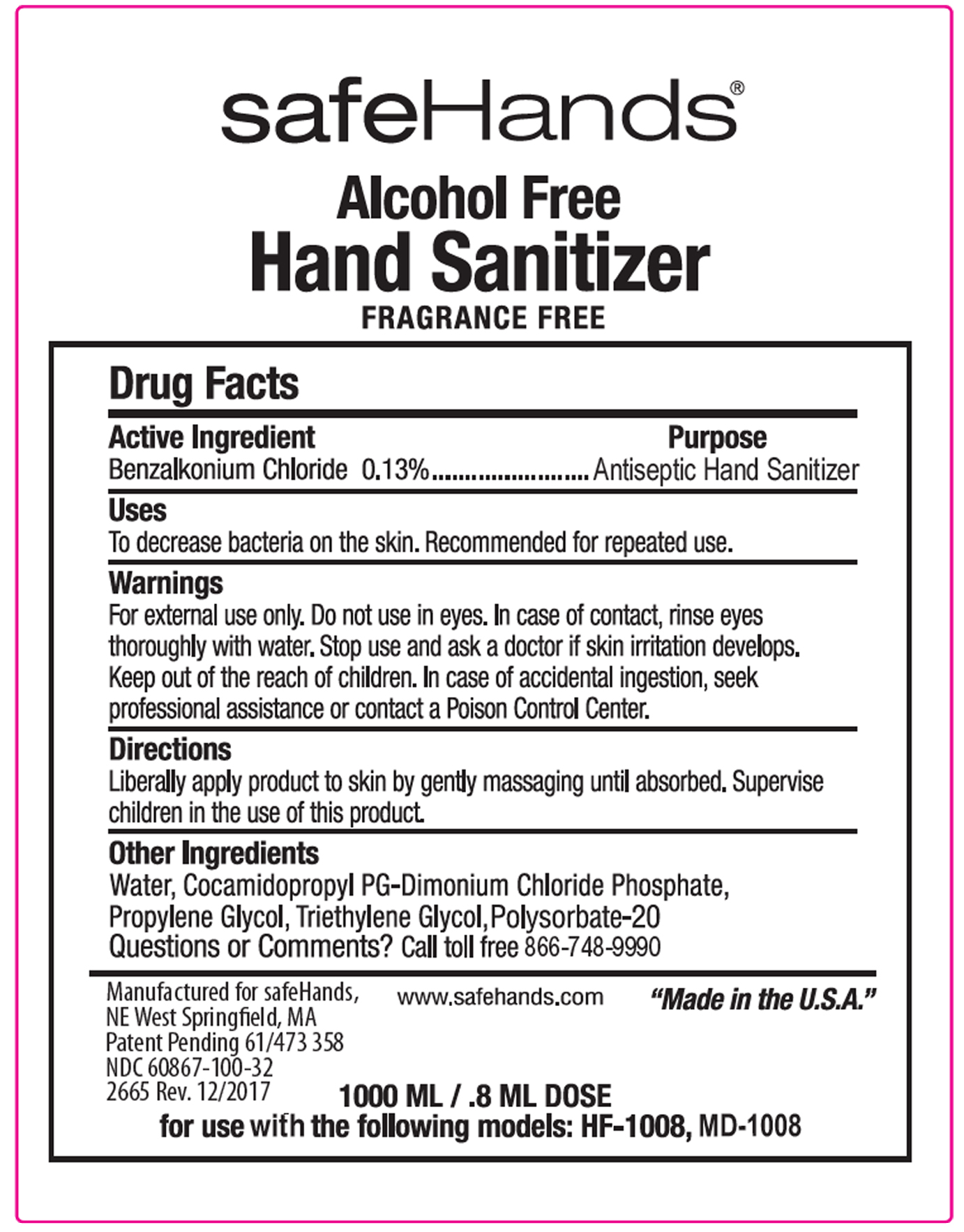 DRUG LABEL: safeHands
NDC: 72646-101 | Form: LIQUID
Manufacturer: Alden Medical LLC
Category: otc | Type: HUMAN OTC DRUG LABEL
Date: 20181108

ACTIVE INGREDIENTS: BENZALKONIUM CHLORIDE 0.13 g/100 mL
INACTIVE INGREDIENTS: WATER

Directions

Liberally apply to skin by gently massaging until absorbed.

Warnings

For external use only. Do not use in eyes. In case of contact, rinse eyes thoroughly with water. Stop use and aska doctor if skin irritation develops.

Inactive Ingredients

Water, Cocamidopropyl PG-Dimonium Chloride Phosphate, Propylene glycol,Triethylene glycol, Polysorbate-20.

Uses

To decrease bacteria on the skin.

Keep out of reach of children.

Purpose

Antiseptic Hand Sanitizer

Active Ingredient

Benzalkonium chloride 0.13%